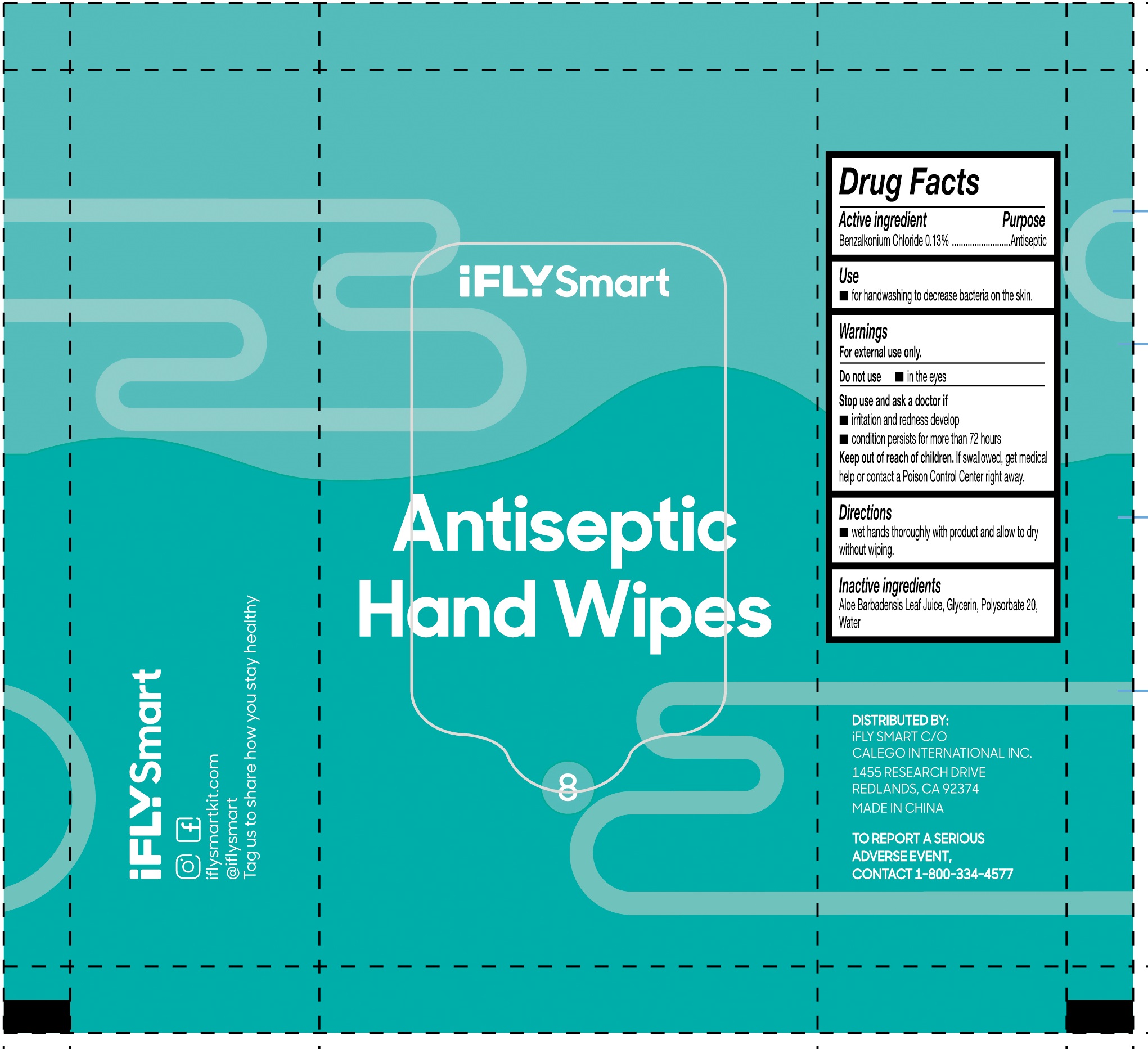 DRUG LABEL: iFLYSmart Antibacterial Hand Wipes
NDC: 76896-006 | Form: CLOTH
Manufacturer: ZHEJIANG BINGER NONWOVEN CO., LTD.
Category: otc | Type: HUMAN OTC DRUG LABEL
Date: 20220115

ACTIVE INGREDIENTS: BENZALKONIUM CHLORIDE 0.13 g/100 g
INACTIVE INGREDIENTS: ALOE VERA LEAF; GLYCERIN; POLYSORBATE 20; WATER

76896-006 iFLYSmart Antiseptic Hand Wipes 0.13%Benzalkonium Chloride

Active Ingredient

Benzalkonium Chloride 0.13%

Prupose

Antiseptic

USE

for handwashing to decrease bacteria on the skin.

Warning

For external use only,
Do not use in the eyes
Stop use and ask a doctor if
irritation and redness develop
condition persists for more than 72 hours

Keep out of reach of children.
If swallowed, get medical help or contact a Poison Control Center right away.

Directions

Wet hands thoroughly with product and allow to dry without wiping

Inactive ingredients

Aloe Barbadensis Leaf Juice, Glycerin, Polysorbate 20,
Water